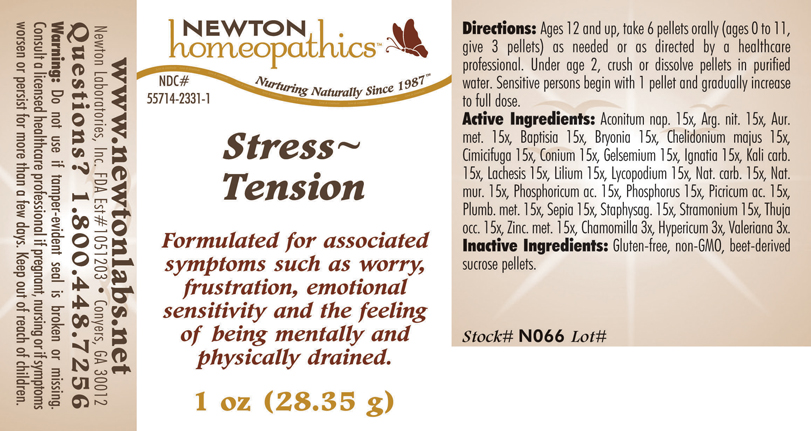 DRUG LABEL: Stress - Tension 
NDC: 55714-2331 | Form: PELLET
Manufacturer: Newton Laboratories, Inc.
Category: homeopathic | Type: HUMAN OTC DRUG LABEL
Date: 20110301

ACTIVE INGREDIENTS: Aconitum Napellus 15 [hp_X]/1 g; Silver Nitrate 15 [hp_X]/1 g; Gold 15 [hp_X]/1 g; Baptisia Tinctoria 15 [hp_X]/1 g; Bryonia Alba Root 15 [hp_X]/1 g; Chelidonium Majus 15 [hp_X]/1 g; Black Cohosh 15 [hp_X]/1 g; Conium Maculatum Flowering Top 15 [hp_X]/1 g; Gelsemium Sempervirens Root 15 [hp_X]/1 g; Strychnos Ignatii Seed 15 [hp_X]/1 g; Potassium Carbonate 15 [hp_X]/1 g; Lachesis Muta Venom 15 [hp_X]/1 g; Lilium Lancifolium Whole Flowering 15 [hp_X]/1 g; Lycopodium Clavatum Spore 15 [hp_X]/1 g; Sodium Carbonate 15 [hp_X]/1 g; Sodium Chloride 15 [hp_X]/1 g; Phosphoric Acid 15 [hp_X]/1 g; Phosphorus 15 [hp_X]/1 g; Trinitrophenol 15 [hp_X]/1 g; Lead 15 [hp_X]/1 g; Sepia Officinalis Juice 15 [hp_X]/1 g; Delphinium Staphisagria Seed 15 [hp_X]/1 g; Datura Stramonium 15 [hp_X]/1 g; Thuja Occidentalis Leafy Twig 15 [hp_X]/1 g; Zinc 15 [hp_X]/1 g; Matricaria Recutita 3 [hp_X]/1 g; Hypericum Perforatum 3 [hp_X]/1 g; Valerian 3 [hp_X]/1 g
INACTIVE INGREDIENTS: Sucrose

Stress - Tension

INDICATIONS & USAGE SECTION

Stress~Tension Formulated for associated symptoms such as worry, frustration, emotional sensitivity and the feeling of being mentally and physically drained.

DOSAGE & ADMINISTRATION SECTION

Directions: Ages 12 and up, take 6 pellets orally (ages 0 to 11, give 3 pellets) as needed or as directed by a healthcare professional. Under age 2, crush or dissolve pellets in purified water. Sensitive persons begin with 1 pellet and gradually increase to full dose.

OTC - ACTIVE INGREDIENT SECTION

Aconitum nap. 15x, Arg. nit. 15x, Aur.met. 15x, Baptisia 15x, Bryonia 15x, Chelidonium majus 15x, Cimicifuga 15x, Conium 15x, Gelsemium 15x, Ignatia 15x, Kali carb.15x, Lachesis 15x, Lilium 15x, Lycopodium 15x, Nat. carb. 15x, Nat.mur. 15x, Phosphoricum ac. 15x, Phosphorus 15x, Picricum ac. 15x, Plumb. met. 15x, Sepia 15x, Staphysag. 15x, Stramonium 15x, Thuja occ. 15x, Zinc. met. 15x, Chamomilla 3x, Hypericum 3x, Valeriana 3x.

OTC - PURPOSE SECTION

Formulated for associated symptoms such as worry, frustration, emotional sensitivity and the feeling of being mentally and physically drained.

INACTIVE INGREDIENT SECTION

Inactive Ingredients: Gluten-free, non-GMO, beet-derived sucrose pellets.

QUESTIONS SECTION

www.newtonlabs.net Newton Laboratories, Inc. FDA Est # 1051203 - Conyers, GA 30012
Questions? 1.800.448.7256

WARNINGS SECTION

Warning: Do not use if tamper - evident seal is broken or missing. Consult a licensed healthcare professional if pregnant, nursing or if symptoms worsen or persist for more than a few days. Keep out of reach of children.

OTC - PREGNANCY OR BREAST FEEDING SECTION

Consult a licensed healthcare professional if pregnant, nursing or if symptoms worsen or persist for more than a few days.

OTC - KEEP OUT OF REACH OF CHILDREN SECTION

Keep out of reach of children.